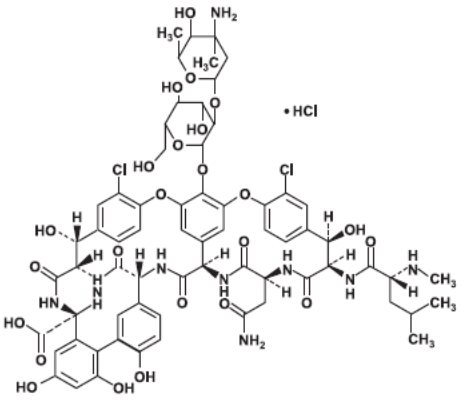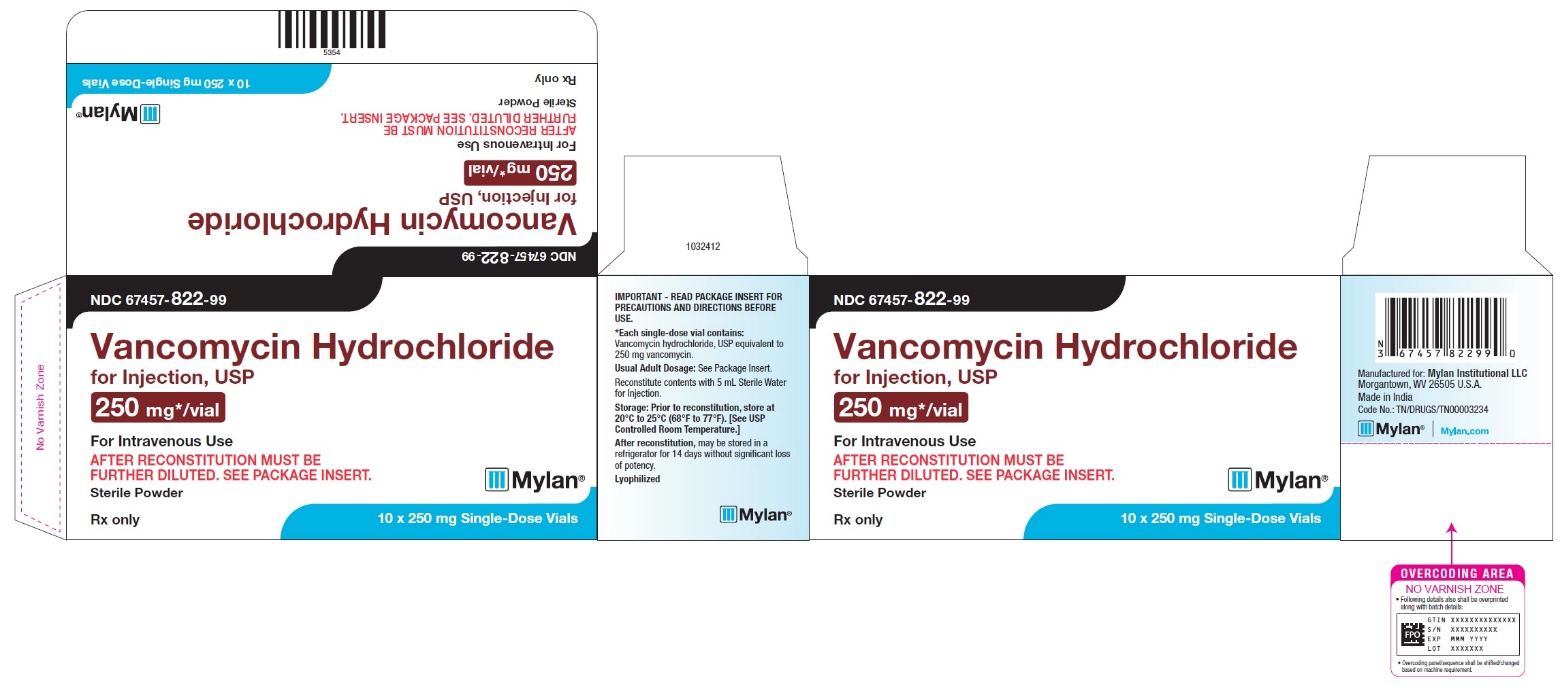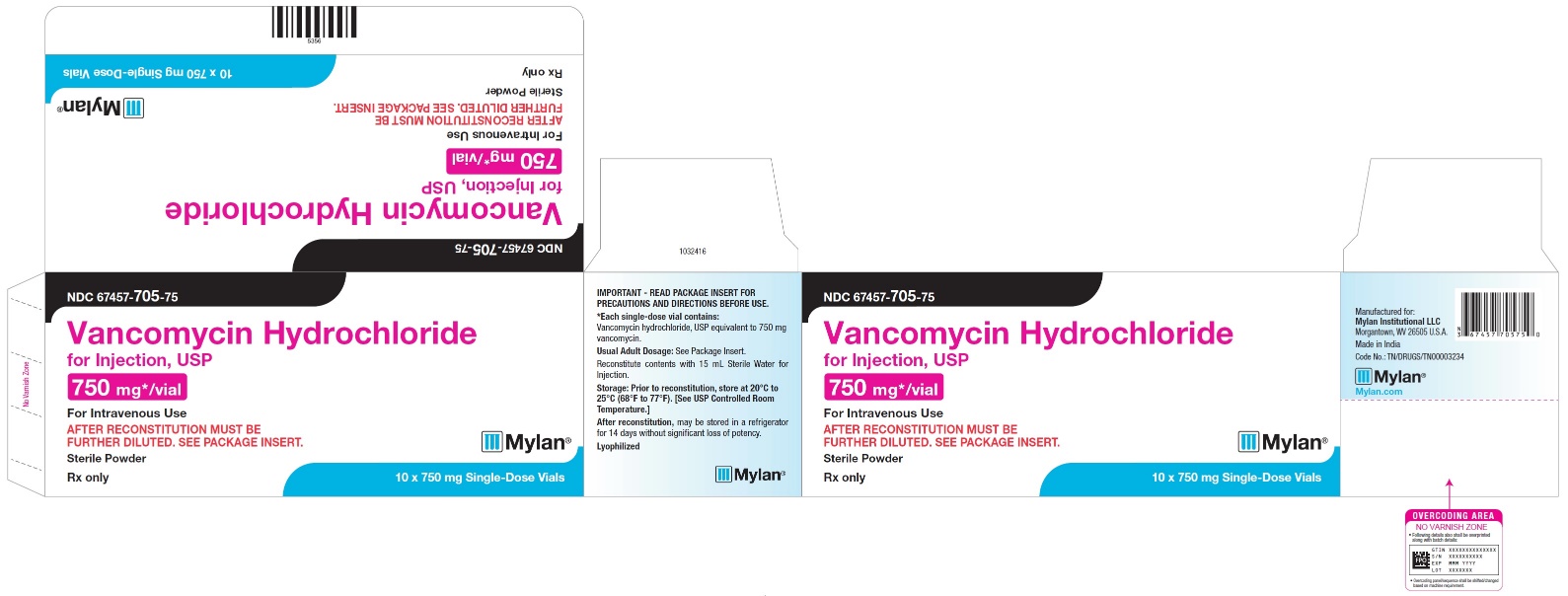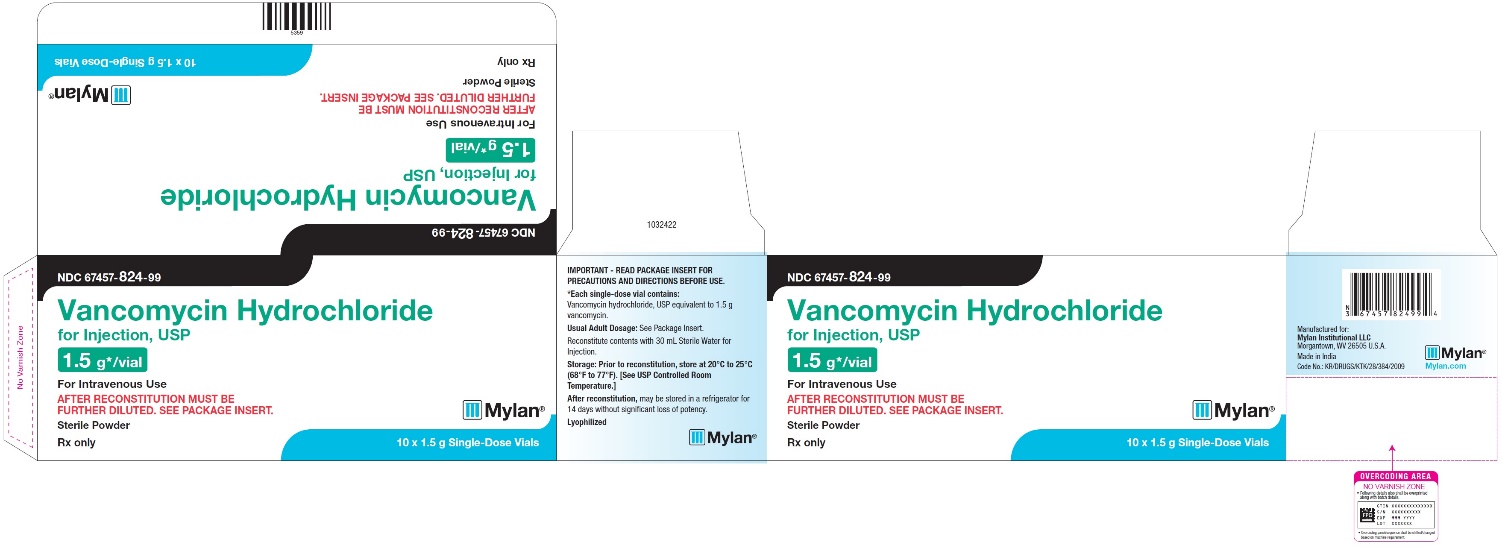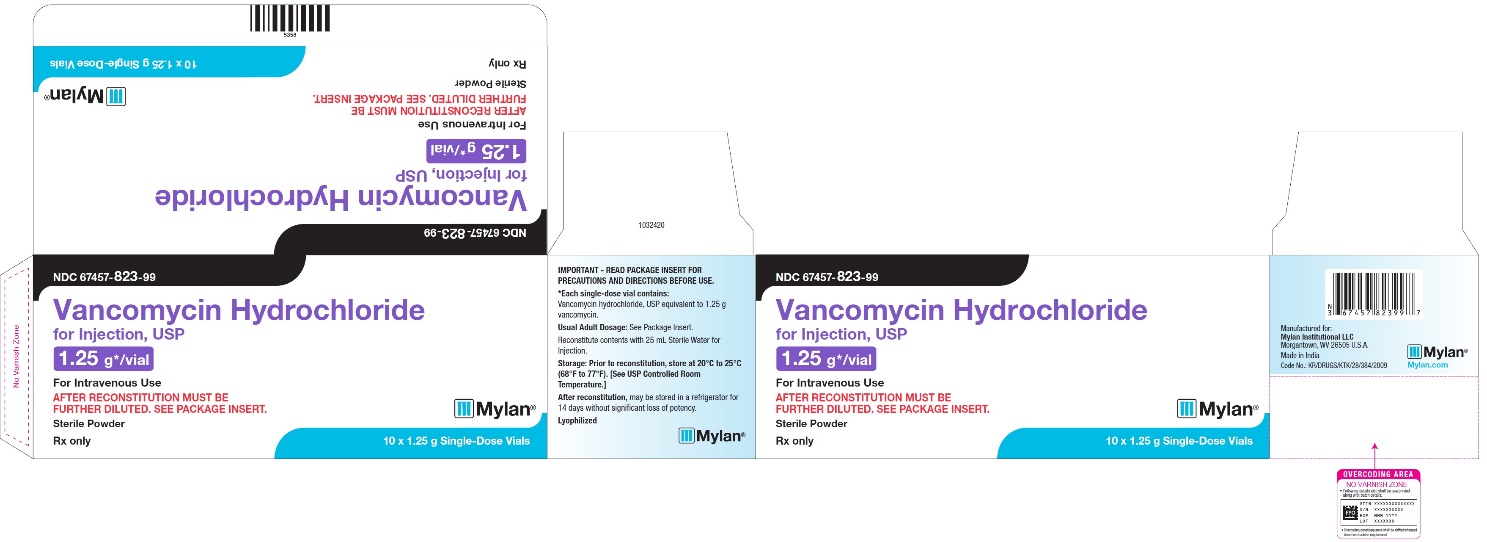 DRUG LABEL: Vancomycin Hydrochloride
NDC: 67457-822 | Form: INJECTION, POWDER, LYOPHILIZED, FOR SOLUTION
Manufacturer: Mylan Institutional LLC
Category: prescription | Type: HUMAN PRESCRIPTION DRUG LABEL
Date: 20240607

ACTIVE INGREDIENTS: VANCOMYCIN HYDROCHLORIDE 250 mg/5 mL

HIGHLIGHTS OF PRESCRIBING INFORMATION

These highlights do not include all the information needed to use VANCOMYCIN HYDROCHLORIDE FOR INJECTION safely and effectively. See full prescribing information for VANCOMYCIN HYDROCHLORIDE FOR INJECTION.
VANCOMYCIN HYDROCHLORIDE for injection, for intravenous use
Initial U.S. Approval: 1958

RECENT MAJOR CHANGES

Dosage and Administration, Preparation of Vancomycin
Hydrochloride for Injection for Intravenous Administration
and Storage Instructions (2.5) 6/2024

1 INDICATIONS AND USAGE

Vancomycin Hydrochloride for Injection is a glycopeptide antibacterial indicated in adult and pediatric patients (neonates and older) for the treatment of:

- Septicemia (1.1)
- Infective Endocarditis (1.2)
- Skin and Skin Structure Infections (1.3)
- Bone Infections (1.4)
- Lower Respiratory Tract Infections (1.5)

To reduce the development of drug-resistant bacteria and maintain the effectiveness of Vancomycin Hydrochloride for Injection and other antibacterial drugs, Vancomycin Hydrochloride for Injection should be used only to treat or prevent infections that are proven or strongly suspected to be caused by susceptible bacteria. (1.6)

2 DOSAGE AND ADMINISTRATION

- Administer Vancomycin Hydrochloride for Injection in a diluted solution over 60 minutes or greater to reduce the risk of infusion reactions.
- See full prescribing information for further important administration and preparation instructions (2.1, 2.5)
- Adult Patients: 2 g divided either as 0.5 grams (g) every 6 hours or 1 g every 12 hours (2.2)
- Pediatric Patients (1 month and older): 10 mg/kg per dose given every 6 hours (2.3)
- Neonates: See full prescribing information for recommended doses in neonates (2.3)
- Patients with renal impairment: See full prescribing information for recommended doses in patients with renal impairment (2.4)

3 DOSAGE FORMS AND STRENGTHS

Vancomycin Hydrochloride for Injection is a sterile lyophilized powder for injection in single-dose vials containing vancomycin hydrochloride, USP equivalent to 250 mg, 750 mg, 1.25 g, 1.5 g, 1.75 g or 2 g of vancomycin base (3)

4 CONTRAINDICATIONS

Hypersensitivity to vancomycin (4)

5 WARNINGS AND PRECAUTIONS

- Infusion Reactions: Hypotension, including shock and cardiac arrest, wheezing, dyspnea, urticaria, muscular, chest pain and “vancomycin infusion reaction” which manifests as pruritus and erythema that involves the face, neck and upper torso may occur with rapid intravenous administration. To reduce the risk of infusion reactions, administer Vancomycin Hydrochloride for Injection in a diluted solution over a period of 60 minutes or greater and also prior to intravenous anesthetic agents. (2.1, 5.1)
- Nephrotoxicity: Systemic vancomycin exposure may result in acute kidney injury (AKI) including acute renal failure, mainly due to interstitial nephritis or less commonly acute tubular necrosis. Monitor serum vancomycin concentrations and renal function. (5.2)
- Ototoxicity: Ototoxicity has occurred in patients receiving vancomycin hydrochloride. Monitor for signs and symptoms of ototoxicity during therapy. Monitor serum vancomycin concentrations and renal function. Assessment of auditory function may be appropriate in some instances. (5.3)
- Severe Dermatologic Reactions: Discontinue Vancomycin Hydrochloride for Injection at the first appearance of skin rashes, mucosal lesions, or blisters (5.4).
- Clostridioides difficile-Associated Diarrhea: Evaluate patients if diarrhea occurs. (5.5)
- Neutropenia: Periodically monitor leukocyte count. (5.7)
- Phlebitis: To reduce the risk of local irritation and phlebitis administer Vancomycin Hydrochloride for Injection by a secure intravenous route of administration. (5.8)
- Development of Drug-Resistant Bacteria: Prescribing Vancomycin Hydrochloride for Injection in the absence of a proven or strongly suspected bacterial infection is unlikely to provide benefit to the patient and increases the risk of the development of drug resistant bacteria. (5.9)

6 ADVERSE REACTIONS

The common adverse reactions are anaphylaxis, “vancomycin infusion reaction”, acute kidney Injury, hearing loss, neutropenia. (6.1)

To report SUSPECTED ADVERSE REACTIONS, contact Mylan at 1-877-446-3679 (1-877-4-INFO-RX) or FDA at 1-800-FDA-1088 or www.fda.gov/medwatch.

7 DRUG INTERACTIONS

- Anesthetic Agents: Concomitant administration of vancomycin and anesthetic agents has been associated with erythema and histamine-like flushing. (2.1, 7.1)
- Piperacillin/Tazobactam: Increased incidence of acute kidney injury in patients receiving concomitant piperacillin/tazobactam and vancomycin as compared to vancomycin alone. Monitor kidney function in patients (7.2)

FULL PRESCRIBING INFORMATION

1 INDICATIONS AND USAGE

1.1 Septicemia

Vancomycin Hydrochloride for Injection is indicated in adults and pediatric patients (neonates and older) for the treatment of septicemia due to:

- Susceptible isolates of methicillin-resistant Staphylococcus aureus (MRSA) and coagulase negative staphylococci.
- Methicillin-susceptible staphylococci in penicillin-allergic patients, or those patients who cannot receive or who have failed to respond to other drugs, including penicillins or cephalosporins.

1.2 Infective Endocarditis

Vancomycin Hydrochloride for Injection is indicated in adults and pediatric patients (neonates and older) for the treatment of infective endocarditis due to:

- Susceptible isolates of MRSA.
- Viridans group streptococci Streptococcus gallolyticus (previously known as Streptococcus bovis), Enterococcus species and Corynebacterium species. For enterococcal endocarditis, use Vancomycin Hydrochloride for Injection in combination with an aminoglycoside.
- Methicillin-susceptible staphylococci in penicillin-allergic patients, or those patients who cannot receive or who have failed to respond to other drugs, including penicillins or cephalosporins.

Vancomycin Hydrochloride for Injection is indicated in adults and pediatric patients (neonates and older) for the treatment of early-onset prosthetic valve endocarditis caused by Staphylococcus epidermidis in combination with rifampin and an aminoglycoside.

1.3 Skin and Skin Structure Infections

Vancomycin Hydrochloride for Injection is indicated in adults and pediatric patients (neonates and older) for the treatment of skin and skin structure infections due to:

- Susceptible isolates of MRSA and coagulase negative staphylococci.
- Methicillin-susceptible staphylococci in penicillin-allergic patients, or those patients who cannot receive or who have failed to respond to other drugs, including penicillins or cephalosporins.

1.4 Bone Infections

Vancomycin Hydrochloride for Injection is indicated in adults and pediatric patients (neonates and older) for the treatment of bone infections due to:

- Susceptible isolates of MRSA and coagulase negative staphylococci.
- Methicillin-susceptible staphylococci in penicillin-allergic patients, or those patients who cannot receive or who have failed to respond to other drugs, including penicillins or cephalosporins.

1.5 Lower Respiratory Tract Infections

Vancomycin Hydrochloride for Injection is indicated in adults and pediatric patients (neonates and older) for the treatment of lower respiratory tract infections due to:

- Susceptible isolates of MRSA
- Methicillin-susceptible staphylococci in penicillin-allergic patients, or those patients who cannot receive or who have failed to respond to other drugs, including penicillins or cephalosporins.

1.6 Usage

To reduce the development of drug-resistant bacteria and maintain the effectiveness of Vancomycin Hydrochloride for Injection and other antibacterial drugs, Vancomycin Hydrochloride for Injection should be used only to treat or prevent infections that are proven or strongly suspected to be caused by susceptible bacteria. When culture and susceptibility information are available, they should be considered in selecting or modifying antibacterial therapy. In the absence of such data, local epidemiology and susceptibility patterns may contribute to the empiric selection of therapy.

2 DOSAGE AND ADMINISTRATION

2.1 Important Administration Instructions

To reduce the risk of infusion related adverse reactions, administer Vancomycin Hydrochloride for Injection in a diluted solution over 60 minutes or greater [see Warnings and Precautions (5.1) and Adverse Reactions (6.1)]. Vancomycin Hydrochloride for Injection concentrations of no more than 5 mg/mL are recommended in adults [see Dosage and Administration (2.2)]. See also age-specific recommendations [see Dosage and Administration (2.3)]. In selected patients in need of fluid restriction, a concentration up to 10 mg/mL may be used [see Warnings and Precautions (5.1)].

Administer Vancomycin Hydrochloride for Injection prior to intravenous anesthetic agents to reduce the risk of infusion related adverse reactions [see Warnings and Precautions (5.1)].

Administer Vancomycin Hydrochloride by a secure intravenous route of administration to avoid local irritation and phlebitis reactions [see Warnings and Precautions (5.8)].

The supplied lyophilized powder must be reconstituted and subsequently diluted prior to intravenous use [see Dosage and Administration (2.5)].

2.2 Dosage in Adult Patients With Normal Renal Function

The usual daily intravenous dose is 2 grams divided either as 500 mg every 6 hours or 1 g every 12 hours. Administer each dose over a period of 60 minutes or greater. Other patient factors, such as age or obesity, may call for modification of the usual intravenous daily dose.

2.3 Dosage in Pediatric Patients With Normal Renal Function

Pediatric Patients (Aged 1 month and older)

The usual intravenous dosage of vancomycin is 10 mg/kg per dose given every 6 hours. Each dose should be administered over a period of at least 60 minutes. Close monitoring of serum concentrations of vancomycin may be warranted in these patients.

Neonates (Up to 1 month old)

In pediatric patients, up to the age of 1 month, the total daily intravenous dosage may be lower. In neonates, an initial dose of 15 mg/kg is suggested, followed by 10 mg/kg every 12 hours for neonates in the 1st week of life and every 8 hours thereafter up to the age of 1 month. Each dose should be administered over 60 minutes. In premature infants, vancomycin clearance decreases as postconceptional age decreases. Therefore, longer dosing intervals may be necessary in premature infants. Close monitoring of serum concentrations of vancomycin is recommended in these patients.

2.4 Dosage in Patients With Renal Impairment

Dosage adjustment must be made in patients with renal impairment. The initial dose should be no less than 15 mg/kg, in patients with any degree of renal impairment.

In premature infants and the elderly, greater dosage reductions than expected may be necessary because of decreased renal function. Measure trough vancomycin serum concentrations to guide therapy, especially in seriously ill patients with changing renal function.

For functionally anephric patients, an initial dose of 15 mg/kg of body weight should be given to achieve prompt therapeutic serum concentration. A dose of 1.9 mg/kg/24 hr should be given after the initial dose of 15 mg/kg.

2.5 Preparation of Vancomycin Hydrochloride for Injection for Intravenous Administration and Storage Instructions

Vancomycin Hydrochloride for Injection must be reconstituted and further diluted.

Reconstitution of the Lyophilized Powder and further dilution

At the time of use, reconstitute the vials of Vancomycin Hydrochloride for Injection (lyophilized powder) with Sterile Water for Injection to a concentration of 50 mg of vancomycin/mL then further dilute with an infusion solution to a final concentration of 5 mg/mL (see Table 1 for the appropriate volumes). Discard any reconstituted solution remaining in the vial.

Table 1 Volume of Sterile Water for Injection to be Added for Reconstitution and Volume of Infusion Solution to be Used for Further Dilution

Vancomycin Strength per Vial | Volume of Sterile Water for Injection for reconstitutiona | Volume of infusion solutionb to further dilute to a final concentration of; 5 mg/mL
250 mg | 5 mL | 50 mL
750 mg | 15 mL | 150 mL
1.25 g | 25 mL | 250 mL
1.5 g | 30 mL | 300 mL
1.75 g | 35 mL | 350 mL
2 g | 40 mL | 400 mL

aAfter reconstitution, the vials may be stored in a refrigerator for 14 days without significant loss of potency.

b Use an infusion solution from the list of the compatible infusion solutions below [see Dosage and Administration (2.6)].

The desired dose diluted in this manner should be administered by intermittent IV infusion over a period of 60 minutes or greater.

Parenteral drug products should be visually inspected for particulate matter and discoloration prior to administration, whenever solution and container permit.

Discard reconstituted and diluted solutions 14 days after initial reconstitution.

2.6 Compatibility with Intravenous Fluids

The following diluents are physically and chemically compatible with 5 g/L vancomycin hydrochloride:

5% Dextrose Injection, USP

5% Dextrose Injection and 0.9% Sodium Chloride Injection, USP

Lactated Ringer’s Injection, USP

Lactated Ringer’s and 5% Dextrose Injection, USP

0.9% Sodium Chloride Injection, USP

Storage of Diluted Solutions:

Solutions that are diluted with 5% Dextrose Injection, USP or 0.9% Sodium Chloride Injection, USP may be stored in a refrigerator for 14 days without significant loss of potency.

Solutions that are diluted with the following infusion fluids may be stored in a refrigerator for 96 hours:

5% Dextrose Injection and 0.9% Sodium Chloride Injection, USP

Lactated Ringer’s Injection, USP

Lactated Ringer’s and 5% Dextrose Injection, USP

2.7 Incompatibilities for Intravenous Use

Vancomycin solution has a low pH and may cause chemical or physical instability when it is mixed with other compounds.

Mixtures of solutions of vancomycin and beta-lactam antibacterial drugs have been shown to be physically incompatible. The likelihood of precipitation increases with higher concentrations of vancomycin. It is recommended to adequately flush the intravenous lines between the administration of these antibacterial drugs. It is also recommended to dilute solutions of vancomycin to 5 mg/mL or less.

3 DOSAGE FORMS AND STRENGTHS

Vancomycin Hydrochloride for Injection, USP is a sterile lyophilized powder for injection supplied as an off-white to light tan colored plug or powder in single-dose vials containing vancomycin hydrochloride, USP equivalent to 250 mg, 750 mg, 1.25 g, 1.5 g, 1.75 g or 2 g of vancomycin base.

4 CONTRAINDICATIONS

Vancomycin Hydrochloride for Injection is contraindicated in patients with known hypersensitivity to vancomycin.

5 WARNINGS AND PRECAUTIONS

5.1 Infusion Reactions

Hypotension, including shock and cardiac arrest, wheezing, dyspnea, urticaria, muscular and chest pain may occur with rapid Vancomycin Hydrochloride for Injection administration. The reactions may be more severe in younger patients, particularly children, and in patients receiving concomitant muscle relaxant anesthetics.

Rapid intravenous administration of Vancomycin Hydrochloride for Injection may also be associated with “vancomycin infusion reaction”, which manifests as pruritus and erythema that involves the face, neck and upper torso.

Infusion-related adverse reactions are related to both the concentration and the rate of administration of vancomycin. Infusion-related adverse reactions may occur, however, at any rate or concentration.

Administer Vancomycin Hydrochloride for Injection in a diluted solution over a period of 60 minutes or greater to reduce the risk of infusion-related adverse reactions. In selected patients in need of fluid restriction, a concentration up to 10 mg/mL may be used; use of such higher concentrations may increase the risk of infusion-related adverse reactions. Administer prior to intravenous anesthetic agents when feasible. Stop the infusion if a reaction occurs.

5.2 Nephrotoxicity

Vancomycin Hydrochloride for Injection can result in acute kidney injury (AKI), including acute renal failure, mainly due to interstitial nephritis or less commonly acute tubular necrosis. AKI is manifested by increasing blood urea nitrogen (BUN) and serum creatinine (Cr). The risk of AKI increases with higher vancomycin serum levels, prolonged exposure, concomitant administration of other nephrotoxic drugs, concomitant administration of piperacillin-tazobactam [see Drug Interactions (7.2)], volume depletion, pre-existing renal impairment and in critically ill patients and patients with co-morbid conditions that predispose to renal impairment.

Monitor serum vancomycin concentrations and renal function in all patients receiving Vancomycin Hydrochloride for Injection. More frequent monitoring is recommended in patients with comorbidities that predispose to impairment in renal function or are concomitantly receiving other nephrotoxic drugs, in critically ill patients, in patients with changing renal function, and in patients requiring higher therapeutic vancomycin levels. If acute kidney injury occurs, discontinue Vancomycin Hydrochloride for Injection or reduce the dose.

5.3 Ototoxicity

Ototoxicity has occurred in patients receiving Vancomycin Hydrochloride for Injection. It may be transient or permanent. Ototoxicity manifests as tinnitus, hearing loss, dizziness or vertigo. The risk is higher in older patients, patients who are receiving higher doses, who have an underlying hearing loss, who are receiving concomitant therapy with another ototoxic agent, such as an aminoglycoside or who have underlying renal impairment. Monitor for signs and symptoms of ototoxicity during therapy. Monitor serum vancomycin concentrations and renal function in all patients receiving parenteral vancomycin. Discontinue Vancomycin Hydrochloride for Injection if ototoxicity occurs. Dosage of Vancomycin Hydrochloride for Injection must be adjusted for patients with renal impairment [see Dosage and Administration (2.3)]. Serial tests of auditory function may be helpful in order to minimize the risk of ototoxicity.

5.4 Severe Dermatologic Reactions

Severe dermatologic reactions such as toxic epidermal necrolysis (TEN), Stevens-Johnson syndrome (SJS), drug reaction with eosinophilia and systemic symptoms (DRESS), acute generalized exanthematous pustulosis (AGEP), and linear IgA bullous dermatosis (LABD) have been reported in association with the use of vancomycin. Cutaneous signs or symptoms reported include skin rashes, mucosal lesions, and blisters.

Discontinue Vancomycin Hydrochloride for Injection at the first appearance of signs and symptoms of TEN, SJS, DRESS, AGEP, or LABD.

5.5 Clostridioides difficile-Associated Diarrhea

Clostridioides difficile-associated diarrhea (CDAD) has been reported with use of nearly all antibacterial agents, including Vancomycin Hydrochloride for Injection, and may range in severity from mild diarrhea to fatal colitis. Treatment with antibacterial agents alters the normal flora of the colon leading to overgrowth of C. difficile.

C. difficile produces toxins A and B which contribute to the development of CDAD. Hypertoxin producing strains of C. difficile cause increased morbidity and mortality, as these infections can be refractory to antimicrobial therapy and may require colectomy. CDAD must be considered in all patients who present with diarrhea following antibacterial use. Careful medical history is necessary since CDAD has been reported to occur over two months after the administration of antibacterial agents.

If CDAD is suspected or confirmed, ongoing antibacterial use not directed against C. difficile may need to be discontinued. Appropriate fluid and electrolyte management, protein supplementation, antibacterial treatment of C. difficile, and surgical evaluation should be instituted as clinically indicated.

Clinically significant serum concentrations have been reported in some patients being treated for active C. difficile-induced pseudomembranous colitis after multiple oral doses of vancomycin.

Prolonged use of Vancomycin Hydrochloride for Injection may result in the overgrowth of nonsusceptible microorganisms. Careful observation of the patient is essential. If superinfection occurs during therapy, appropriate measures should be taken. In rare instances, there have been reports of pseudomembranous colitis due to C. difficile developing in patients who received intravenous Vancomycin Hydrochloride for Injection.

5.6 Hemorrhagic Occlusive Retinal Vasculitis (HORV)

Hemorrhagic occlusive retinal vasculitis, including permanent loss of vision, occurred in patients receiving intracameral or intravitreal administration of vancomycin during or after cataract surgery. The safety and efficacy of vancomycin administered by the intracameral or the intravitreal route have not been established by adequate and well-controlled trials. Vancomycin is not indicated for the prophylaxis of endophthalmitis.

5.7 Neutropenia

Reversible neutropenia has been reported in patients receiving Vancomycin Hydrochloride for Injection [see Adverse Reactions (6.1)]. Patients who will undergo prolonged therapy with Vancomycin Hydrochloride for Injection or those who are receiving concomitant drugs which may cause neutropenia should have periodic monitoring of the leukocyte count.

5.8 Phlebitis and Other Administration Site Reactions

Inflammation at the site of injection of Vancomycin Hydrochloride for Injection has been reported. Vancomycin Hydrochloride for Injection is irritating to tissue and must be given by a secure intravenous route of administration to reduce the risk of local irritation and phlebitis.

Administration of Vancomycin Hydrochloride for Injection by intramuscular (IM), intraperitoneal, intrathecal (intralumbar or intraventricular), or intravitreal routes has not been approved and is not recommended. The safety and efficacy of vancomycin administered by the intrathecal (intralumbar or intraventricular) route or by the intraperitoneal route have not been established by adequate and well controlled trials.

Pain, tenderness, and necrosis occur with IM injection of Vancomycin Hydrochloride for Injection or with inadvertent extravasation. Thrombophlebitis may occur, the frequency and severity of which can be minimized by administering the drug slowly as a dilute solution (2.5 to 5 g/L) and by rotation of venous access sites.

Intraperitoneal administration during continuous ambulatory peritoneal dialysis (CAPD) can result in chemical peritonitis. Manifestations range from cloudy dialysate alone to a cloudy dialysate accompanied by variable degrees of abdominal pain and fever. This syndrome appears to be resolve after discontinuation of intraperitoneal vancomycin.

5.9 Development of Drug-Resistant Bacteria

Prescribing Vancomycin Hydrochloride for Injection in the absence of a proven or strongly suspected bacterial infection or a prophylactic indication is unlikely to provide benefit to the patient and increases the risk of the development of drug-resistant bacteria.

6 ADVERSE REACTIONS

The following clinically significant adverse reactions are described elsewhere in the labeling:

- Infusion Reactions [see Warnings and Precautions (5.1)]
- Nephrotoxicity [see Warnings and Precautions (5.2)]
- Ototoxicity [see Warnings and Precautions (5.3)]
- Clostridioides difficile-Associated Diarrhea [see Warnings and Precautions (5.5)]
- Hemorrhagic Occlusive Retinal Vasculitis [see Warnings and Precautions (5.6)]
- Neutropenia [see Warnings and Precautions (5.7)]

6.1 Clinical Trials Experience

Because clinical trials are conducted under widely varying conditions, adverse reaction rates observed in the clinical trials of a drug cannot be directly compared to rates in the clinical trials of another drug and may not reflect the rates observed in practice.

The following adverse reactions associated with the use of Vancomycin Hydrochloride for Injection were identified in clinical trials:

Immune system disorders: Hypersensitivity reactions including anaphylaxis and “vancomycin infusion reaction” [see Warnings and Precautions (5.1)]

Skin and subcutaneous tissue disorders: Erythema (especially of the face, neck and upper torso) and pruritus which are manifestations of rashes including exfoliative dermatitis, toxic epidermal necrolysis (TEN), Stevens-Johnson syndrome (SJS), Linear IgA bullous dermatosis (LABD) [see Warnings and Precautions (5.4)].

Renal and urinary disorders: Acute kidney injury and interstitial nephritis

Ear and Labyrinth Disorders: Tinnitus, hearing loss, vertigo

Blood and Lymphatic System Disorders: Agranulocytosis, neutropenia, pancytopenia, leukopenia, thrombocytopenia, eosinophilia

Gastrointestinal Disorders: Pseudomembranous colitis [see Warnings and Precautions (5.5)]

Cardiac Disorders: Cardiac arrest, chest pain

General Disorders and Administration Site Conditions: General discomfort, fever, chills, phlebitis, injection site irritation, injection site pain and necrosis following intramuscular injection, chemical peritonitis following intraperitoneal administration

(Vancomycin Hydrochloride for Injection is not approved for intramuscular and intraperitoneal administration) [see Warnings and Precautions (5.7)]

Laboratory Abnormalities: Elevated blood urea nitrogen, elevated serum creatinine

Musculoskeletal and connective tissue disorders: Muscle pain

Nervous system disorders: Dizziness

Respiratory, thoracic and mediastinal disorders: Wheezing, dyspnea

Vascular disorders: Hypotension, shock, vasculitis

6.2 Postmarketing Experience

The following adverse reactions have been identified during post approval use of vancomycin. Because these reactions are reported voluntarily from a population of uncertain size, it is not possible to reliably estimate their frequency or establish a causal relationship to drug exposure.

Skin and Subcutaneous Tissue Disorders: Drug reaction with eosinophilia and systemic symptoms (DRESS), acute generalized exanthematous pustulosis (AGEP) [see Warnings and Precautions (5.4)].

7 DRUG INTERACTIONS

7.1 Anesthetic Agents

Concomitant administration of vancomycin and anesthetic agents has been associated with erythema and histamine-like flushing [see Warnings and Precautions (5.1)and Use in Specific Populations (8.4)].

7.2 Piperacillin-Tazobactam

Studies have detected an increased incidence of acute kidney injury in patients administered concomitant piperacillin/tazobactam and vancomycin as compared to vancomycin alone. Monitor kidney function in patients receiving concomitant piperacillin/tazobactam and vancomycin. No pharmacokinetic interactions have been noted between piperacillin/tazobactam and vancomycin.

7.3 Ototoxic and/or Nephrotoxic Drugs

Concurrent and/or sequential systemic or topical use of other potentially, neurotoxic and/or nephrotoxic drugs requires more frequent monitoring of renal function.

8 USE IN SPECIFIC POPULATIONS

8.1 Pregnancy

Risk Summary

There are no available data on vancomycin use in pregnant women to inform a drug associated risk of major birth defects or miscarriage. Available published data on vancomycin use in pregnancy during the second and third trimesters have not shown an association with adverse pregnancy related outcomes (see Data). Vancomycin did not show adverse developmental effects when administered intravenously to pregnant rats and rabbits during organogenesis at doses less than or equal to the recommended maximum human dose based on body surface area (see Data).

All pregnancies have a background risk of birth defect, loss, or other adverse outcomes. In the U.S. general population, the estimated background risk of major birth defects and miscarriage in clinically recognized pregnancies is 2 to 4% and 15 to 20%, respectively.

Data

Human Data

A published study evaluated hearing loss and nephrotoxicity in infants of pregnant intravenous drug users treated with vancomycin for suspected or documented methicillin-resistant Staphylococcus-aureus in the second or third trimester. The comparison groups were 10 non-intravenous drug-dependent patients who received no treatment, and 10 untreated intravenous drug-dependent patients who served as substance abuse controls. No infant in the vancomycin exposed group had abnormal sensorineural hearing at 3 months of age or nephrotoxicity.

A published prospective study assessed outcomes in 55 pregnant women with a positive Group B streptococcus (GBS) culture and a high-risk penicillin allergy with resistance to clindamycin or unknown sensitivity who were administered vancomycin at the time of delivery. Vancomycin dosing ranged from the standard 1 g intravenously every 12 hours to 20 mg/kg intravenous every 8 hours (maximum individual dose 2 g). No major adverse reactions were recorded either in the mothers or their newborns. None of the newborns had sensorineural hearing loss. Neonatal renal function was not examined, but all of the newborns were discharged in good condition.

Animal Data

Vancomycin did not cause fetal malformations when administered during organogenesis to pregnant rats (gestation days 6 to 15) and rabbits (gestation days 6 to 18) at the equivalent recommended maximum human dose (based on body surface area comparisons) of 200 mg/kg/day IV to rats or 120 mg/kg/day IV to rabbits. No effects on fetal weight or development were seen in rats at the highest dose tested or in rabbits given 80 mg/kg/day (approximately 1 and 0.8 times the recommended maximum human dose based on body surface area, respectively). Maternal toxicity was observed in rats (at doses 120 mg/kg and above) and rabbits (at 80 mg/kg and above).

8.2 Lactation

Risk Summary

There are insufficient data to inform the levels of vancomycin in human milk. There are no data on the effects of vancomycin on the breastfed infant or milk production. The developmental and health benefits of breastfeeding should be considered along with the mother’s clinical need for vancomycin and any potential adverse effects on the breastfed infant from vancomycin or from the underlying maternal condition.

8.4 Pediatric Use

Vancomycin Hydrochloride for Injection is indicated in pediatric patients (neonates and older). In pediatric patients, monitor vancomycin serum concentration and renal function when administering Vancomycin Hydrochloride for Injection [see Dosage and Administration (2.2, 2.3) and Warnings and Precautions (5.2)]. More severe infusion related reactions related to vancomycin administration may occur in pediatric patients. Concomitant administration of vancomycin and intravenous anesthetic agents has been associated with erythema and histamine-like flushing in all patients including pediatric patients [see Warnings and Precautions (5.1)].

8.5 Geriatric Use

Vancomycin Hydrochloride for Injection is known to be substantially excreted by the kidney, and the risk of adverse reactions to this drug may be greater in patients with impaired renal function. Because elderly patients are more likely to have decreased renal function, care should be taken in dose selection [see Dosage and Administration (2.2)], and it may be useful to monitor renal function [see Warnings and Precautions (5.2)].

10 OVERDOSAGE

Supportive care is advised, with maintenance of glomerular filtration. Vancomycin is poorly removed by dialysis. Hemofiltration and hemoperfusion with polysulfone resin have been reported to result in increased vancomycin clearance.

For current information on the management of overdosage, contact the National Poison Control Center at 1-800-222-1222 or www.poison.org.

11 DESCRIPTION

Vancomycin Hydrochloride for Injection, USP, contains the hydrochloride salt of vancomycin, a tricyclic glycopeptide antibacterial derived from Amycolatopsis orientalis (formerly Nocardia orientalis). The chemical name for vancomycin hydrochloride, USP is (Sa)-(3S,6R,7R,22R,23S,26S,36R,38aR)-44-[[2-O-(3-Amino-2,3,6-trideoxy-3-C-methyl-α-L-lyxo-hexopyranosyl)-β-D-glucopyranosyl]oxy]-3-(carbamoylmethyl)-10,19-dichloro-2,3,4,5,6,7,23,24,25,26,36,37,38,38a-tetradecahydro-7,22,28,30,32-pentahydroxy-6-[(2R)-4-methyl-2-(methylamino)valeramido]-2, 5, 24,38,39-pentaoxo-22H-8,11:18,21-dietheno-23,36-(iminomethano)-13,16:31,35-dimetheno-1H,16H-[l, 6,9]oxadiazacyclohexadecino[4,5-m][10,2,16]-benzoxadiazacyclotetracosine-26-carboxylic acid, monohydrochloride. The molecular formula is C66H75Cl2N9O24 • HCl and the molecular weight is 1,485.71. Vancomycin hydrochloride, USP has the following structural formula:

Vancomycin Hydrochloride for Injection, USP is a sterile off-white to light tan colored lyophilized plug or powder for injection. Vancomycin Hydrochloride for Injection, USP is supplied in single-dose vials, containing 256 mg, 769 mg, 1.28 g, 1.54 g, 1.79 g or 2.05 g of vancomycin hydrochloride, USP equivalent to 250 mg, 750 mg, 1.25 g, 1.5 g, 1.75 g or 2 g of vancomycin base. The lyophilized powder is reconstituted with Sterile Water for Injection, USP which forms a clear, colorless or light to dark tan solution and subsequently diluted prior to intravenous administration [see Dosage and Administration (2.5)].

12 CLINICAL PHARMACOLOGY

12.1 Mechanism of Action

Vancomycin is an antibacterial drug [see Microbiology (12.4)].

12.2 Pharmacodynamics

The pharmacodynamics of vancomycin is unknown.

12.3 Pharmacokinetics

In subjects with normal kidney function, multiple intravenous dosing of 1 g of vancomycin (15 mg/kg) infused over 60 minutes produces mean plasma concentrations of approximately 63 mcg/mL immediately after the completion of infusion, mean plasma concentrations of approximately 23 mcg/mL 2 hours after infusion, and mean plasma concentrations of approximately 8 mcg/mL 11 hours after the end of the infusion. Multiple dosing of 500 mg infused over 30 minutes produces mean plasma concentrations of about 49 mcg/mL at the completion of infusion, mean plasma concentrations of about 19 mcg/mL 2 hours after infusion, and mean plasma concentrations of about 10 mcg/mL 6 hours after infusion. The plasma concentrations during multiple dosing are like those after a single dose.

Distribution

The volume of distribution ranges from 0.3 to 0.43 L/kg after intravenous administration. Vancomycin is approximately 55% serum protein bound as measured by ultrafiltration at vancomycin serum concentrations of 10 to 100 mcg/mL. After intravenous administration of vancomycin, inhibitory concentrations are present in pleural, pericardial, ascitic, and synovial fluids; in urine; in peritoneal dialysis fluid; and in atrial appendage tissue. Vancomycin does not readily diffuse across normal meninges into the spinal fluid; but, when the meninges are inflamed, penetration into the spinal fluid occurs.

Elimination

Mean plasma clearance is about 0.058 L/kg/h, and mean renal clearance is about 0.048 L/kg/h.

The mean elimination half-life of vancomycin from plasma is 4 to 6 hours in subjects with normal renal function. In anephric patients, the mean elimination half-life is 7.5 days. Total body and renal clearance of vancomycin may be reduced in the elderly.

Metabolism

There is no apparent metabolism of the vancomycin.

Excretion

In the first 24 hours after intravenous administration, about 75% of an administered dose of vancomycin is excreted in urine by glomerular filtration. Renal impairment slows excretion of vancomycin.

About 60% of an intraperitoneal dose of vancomycin administered during peritoneal dialysis is absorbed systemically in 6 hours. Serum concentrations of about 10 mcg/mL are achieved by intraperitoneal injection of 30 mg/kg of vancomycin. However, the safety and efficacy of the intraperitoneal use of vancomycin has not been established in adequate and well-controlled trials [see Warnings and Precautions (5.7)].

12.4 Microbiology

Mechanism of Action

The bactericidal action of vancomycin results primarily from inhibition of cell-wall biosynthesis. In addition, vancomycin alters bacterial-cell-membrane permeability and RNA synthesis.

Resistance

Vancomycin is not active in vitro against gram-negative bacilli, mycobacteria, or fungi. There is no cross-resistance between vancomycin and other antibacterials.

Interaction With Other Antimicrobials

The combination of vancomycin and an aminoglycoside acts synergistically in vitro against many isolates of Staphylococcus aureus, Streptococcus gallolyticus (previously known as Streptococcus bovis), enterococcus spp, and the viridans group streptococci.

Antimicrobial Activity

Vancomycin has been shown to be active against most isolates of the following microorganisms, both in vitro and in clinical infections [see Indications and Usage (1)].

Aerobic Gram-Positive Bacteria

Corynebacterium spp.

Enterococcus spp. (including Enterococcus faecalis)

Staphylococcus aureus (including methicillin-resistant and methicillin-susceptible isolates)

Coagulase negative staphylococci (including S. epidermidis and methicillin-resistant isolates)

Streptococcus gallolyticus (previously known as Streptococcus bovis)

Viridans group streptococci

The following in vitro data are available, but their clinical significance is unknown. At least 90 percent of the following bacteria exhibit an in vitro minimum inhibitory concentration (MIC) less than or equal to the susceptible breakpoint for vancomycin against isolates of similar genus or organism group. However, the efficacy of vancomycin in treating clinical infections caused by these bacteria has not been established in adequate and well-controlled clinical trials.

Aerobic Gram-Positive Bacteria

Listeria monocytogenes

Streptococcus pyogenes

Streptococcus pneumoniae

Streptococcus agalactiae

Anaerobic Gram-Positive Bacteria

Actinomyces species

Lactobacillus species

Susceptibility Testing

For specific information regarding susceptibility test interpretive criteria and associated test methods and quality control standards recognized by FDA for this drug, please see: https://www.fda.gov/STIC.

13 NONCLINICAL TOXICOLOGY

13.1 Carcinogenesis, Mutagenesis, Impairment of Fertility

Although no long-term studies in animals have been performed to evaluate carcinogenic potential, no mutagenic potential of Vancomycin Hydrochloride for Injection was found in standard laboratory tests. No definitive fertility studies have been performed.

13.2 Animal Toxicology and/or Pharmacology

In animal studies, hypotension and bradycardia occurred in dogs receiving an intravenous infusion of vancomycin hydrochloride 25 mg/kg, at a concentration of 25 mg/mL and an infusion rate of 13.3 mL/min.

15 REFERENCES

1. Byrd RA., Gries CL, Buening M.: Developmental Toxicology Studies of Vancomycin Hydrochloride Administered Intravenously to Rats and Rabbits. Fundam Appl Toxicol 1994; 23: 590-597.

16 HOW SUPPLIED/STORAGE AND HANDLING

How Supplied:

Vancomycin Hydrochloride for Injection, USP is a sterile lyophilized powder for injection supplied as an off-white to light tan colored powder or plug in single-dose flip top vials that contain vancomycin hydrochloride, USP equivalent to 250 mg, 750 mg, 1.25 g, 1.5 g, 1.75 g or 2 g of vancomycin base. They are available as follows:

NDC No. 67457-822-99: Vancomycin Hydrochloride for Injection, USP equivalent to 250 mg vancomycin in a 5 mL flip top vial with an ash gray seal, in packages of 10 vials.

NDC No. 67457-705-75: Vancomycin Hydrochloride for Injection, USP equivalent to 750 mg vancomycin in a 20 mL flip top vial with an ash gray seal, in packages of 10 vials.

NDC No. 67457-823-99: Vancomycin Hydrochloride for Injection, USP equivalent to 1.25 g vancomycin in a 30 mL flip top vial with an ash gray seal, in packages of 10 vials.

NDC No. 67457-824-99: Vancomycin Hydrochloride for Injection, USP equivalent to 1.5 g vancomycin in a 30 mL flip top vial with a golden brown seal, in packages of 10 vials.

NDC No. 72078-065-50: Vancomycin Hydrochloride for Injection, USP equivalent to 1.75 g vancomycin in a 50 mL flip top vial with a grey seal, in packages of 1 vial.

NDC No. 72078-065-99: Vancomycin Hydrochloride for Injection, USP equivalent to 1.75 g vancomycin in a 50 mL flip top vial with a grey seal, in packages of 10 vials.

NDC No. 72078-066-50: Vancomycin Hydrochloride for Injection, USP equivalent to 2 g vancomycin in a 50 mL flip top vial with a pink seal, in packages of 1 vial.

NDC No. 72078-066-99: Vancomycin Hydrochloride for Injection, USP equivalent to 2 g vancomycin in a 50 mL flip top vial with a pink seal, in packages of 10 vials.

Storage:

Prior to reconstitution, store at 20°C to 25°C (68°F to 77°F); excursions permitted to 15°C to 30°C (59°F to 86°F). [See USP Controlled Room Temperature.]

17 PATIENT COUNSELING INFORMATION

Infusion Reactions During or After Intravenous Use

Advise patients that generalized skin redness, skin rash, itching, flushing, muscle pain, chest pain, shortness of breath, wheezing, or dizziness may occur during intravenous infusion of Vancomycin Hydrochloride for Injection. These reactions can be lessened or prevented by infusing the drug over at least 60 minutes [see Warnings and Precautions (5.1)].

Acute Kidney Injury

Advise patients that Vancomycin Hydrochloride for Injection can result in kidney damage and that blood tests are required to monitor vancomycin blood levels and kidney function during therapy [see Warnings and Precautions (5.2)].

Hearing Loss or Balance Problems

Advise patients that Vancomycin Hydrochloride for Injection may result in decreased hearing and to report hearing loss or balance problems to their healthcare provider [see Warnings and Precautions (5.3)].

Severe Dermatologic Reactions

Advise patients about the signs and symptoms of serious skin manifestations. Instruct patients to stop Vancomycin Hydrochloride for Injection immediately and promptly seek medical attention at the first signs or symptoms of skin rash, mucosal lesions or blisters [see Warnings and Precautions (5.4)].

Antibacterial Resistance

Patients should be counseled that antibacterial drugs including Vancomycin Hydrochloride for Injection should only be used to treat bacterial infections. They do not treat viral infections (e.g., the common cold). When Vancomycin Hydrochloride for Injection is prescribed to treat a bacterial infection, patients should be told that although it is common to feel better early in the course of therapy, the medication should be taken exactly as directed. Skipping doses or not completing the full course of therapy may (1) decrease the effectiveness of the immediate treatment and (2) increase the likelihood that bacteria will develop resistance and will not be treatable by Vancomycin Hydrochloride for Injection or other antibacterial drugs in the future.

Diarrhea

Diarrhea is a common problem caused by antibacterial drugs, including vancomycin, which usually ends when the antibacterial drug is discontinued. Sometimes after starting treatment with antibacterial drugs, patients can develop watery and bloody stools (with or without stomach cramps and fever) even as late as two or more months after having taken the last dose of the antibacterial drug. If this occurs, patients should contact their physician as soon as possible [see Warnings and Precautions (5.5)].

The brands listed are trademarks of their respective owners.

Manufactured for:

Mylan Institutional LLC

Morgantown, WV 26505 U.S.A.

Manufactured by:

Mylan Laboratories Limited

Bangalore, India

PRINCIPAL DISPLAY PANEL – 250 mg

NDC 67457-822-99

Vancomycin Hydrochloride
for Injection, USP

250 mg*/vial

For Intravenous Use

AFTER RECONSTITUTION MUST BE FURTHER DILUTED.
SEE PACKAGE INSERT.

Sterile Powder

Rx only

Mylan

10 x 250 mg Single-Dose Vials

IMPORTANT - READ PACKAGE INSERT FOR
PRECAUTIONS AND DIRECTIONS BEFORE
USE.

*Each single-dose vial contains:
Vancomycin hydrochloride, USP equivalent to
250 g vancomycin.

Usual Adult Dosage: See Package Insert.

Reconstitute contents with 5 mL Sterile Water
for Injection.

Storage: Prior to reconstitution, store at
20°C to 25°C (68°F to 77°F). [See USP
Controlled Room Temperature.]

After reconstitution, may be stored in a
refrigerator for 14 days without significant loss
of potency.

Lyophilized

Manufactured for:
Mylan Institutional LLC
Morgantown, WV 26505 U.S.A.

Made in India

Code No.: TN/DRUGS/TN00003234

Mylan.com

PRINCIPAL DISPLAY PANEL – 750 mg

NDC 67457-705-75

Vancomycin Hydrochloride
for Injection, USP

750 mg*/vial

For Intravenous Use

AFTER RECONSTITUTION MUST
BE FURTHER DILUTED. SEE PACKAGE INSERT.

Sterile Powder

Rx only

Mylan

10 x 750 mg Single-Dose Vials

IMPORTANT - READ PACKAGE INSERT FOR
PRECAUTIONS AND DIRECTIONS BEFORE USE.

*Each single-dose vial contains:
Vancomycin hydrochloride, USP equivalent to 750 g
vancomycin.

Usual Adult Dosage: See Package Insert.

Reconstitute contents with 15 mL Sterile Water for
Injection.

Storage: Prior to reconstitution, store at 20°C to
25°C (68°F to 77°F). [See USP Controlled Room
Temperature.]

After reconstitution, may be stored in a refrigerator
for 14 days without significant loss of potency.

Lyophilized

Manufactured for:
Mylan Institutional LLC
Morgantown, WV 26505 U.S.A.

Made in India

Code No.: TN/DRUGS/TN00003234

Mylan.com

PRINCIPAL DISPLAY PANEL – 1.25 g

NDC 67457-823-99

Vancomycin Hydrochloride
for Injection, USP

1.25 g*/vial

For Intravenous Use

AFTER RECONSTITUTION MUST
BE FURTHER DILUTED. SEE PACKAGE INSERT.

Sterile Powder

Rx only

Mylan

10 x 1.25 g Single-Dose Vials

IMPORTANT - READ PACKAGE INSERT FOR
PRECAUTIONS AND DIRECTIONS BEFORE USE.

*Each single-dose vial contains:
Vancomycin hydrochloride, USP equivalent to 1.25 g
vancomycin.

Usual Adult Dosage: See Package Insert.

Reconstitute contents with 25 mL Sterile Water for
Injection.

Storage: Prior to reconstitution, store at 20°C to 25°C
(68°F to 77°F). [See USP Controlled Room
Temperature.]

After reconstitution, may be stored in a refrigerator for
14 days without significant loss of potency.

Lyophilized

Manufactured for:
Mylan Institutional LLC
Morgantown, WV 26505 U.S.A.

Made in India

Code No.: TN/DRUGS/KTG/28/384/2009

Mylan.com

PRINCIPAL DISPLAY PANEL – 1.5 g

NDC 67457-824-99

Vancomycin Hydrochloride
for Injection, USP

1.5 g*/vial

For Intravenous Use

AFTER RECONSTITUTION MUST BE
FURTHER DILUTED. SEE PACKAGE INSERT.

Sterile Powder

Rx only

Mylan

10 x 1.5 g Single-Dose Vials

IMPORTANT - READ PACKAGE INSERT FOR
PRECAUTIONS AND DIRECTIONS BEFORE USE.

*Each single-dose vial contains:
Vancomycin hydrochloride, USP equivalent to 1.5 g
vancomycin.

Usual Adult Dosage: See Package Insert.

Reconstitute contents with 30 mL Sterile Water for
Injection.

Storage: Prior to reconstitution, store at 20°C to 25°C
(68°F to 77°F). [See USP Controlled Room
Temperature.]

After reconstitution, may be stored in a refrigerator for
14 days without significant loss of potency.

Lyophilized

Manufactured for:
Mylan Institutional LLC
Morgantown, WV 26505 U.S.A.

Made in India

Code No.: TN/DRUGS/KTG/28/384/2009

Mylan.com